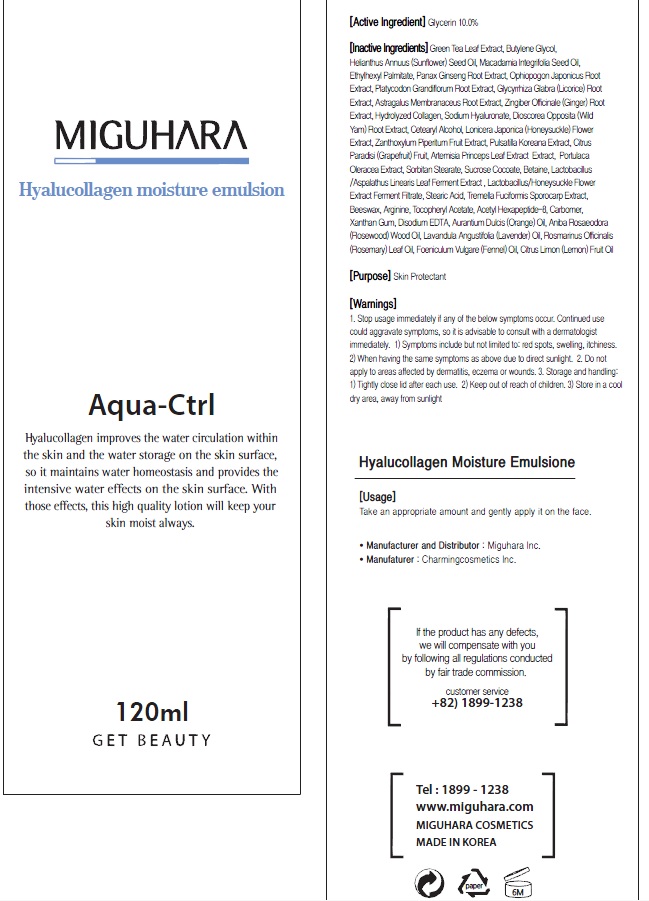 DRUG LABEL: Hyalucollagen Moisture
NDC: 70380-200 | Form: EMULSION
Manufacturer: MIGUHARA
Category: otc | Type: HUMAN OTC DRUG LABEL
Date: 20160222

ACTIVE INGREDIENTS: Glycerin 12.0 g/120 mL
INACTIVE INGREDIENTS: GREEN TEA LEAF; Butylene Glycol

ACTIVE INGREDIENT

Active Ingredient: Glycerin 10.0%

INACTIVE INGREDIENT

Inactive Ingredients: Green Tea Leaf Extract, Butylene Glycol, Helianthus Annuus (Sunflower) Seed Oil, Macadamia Integrifolia Seed Oil, Ethylhexyl Palmitate, Panax Ginseng Root Extract, Ophiopogon Japonicus Root Extract, Platycodon Grandiflorum Root Extract, Glycyrrhiza Glabra (Licorice) Root Extract, Astragalus Membranaceus Root Extract, Zingiber Officinale (Ginger) Root Extract, Hydrolyzed Collagen, Sodium Hyaluronate, Dioscorea Opposita (Wild Yam) Root Extract, Cetearyl Alcohol, Lonicera Japonica (Honeysuckle) Flower Extract, Zanthoxylum Piperitum Fruit Extract, Pulsatilla Koreana Extract, Citrus Paradisi (Grapefruit) Fruit, Artemisia Princeps Leaf Extract Extract, Portulaca Oleracea Extract, Sorbitan Stearate, Sucrose Cocoate, Betaine, Lactobacillus/Aspalathus Linearis Leaf Ferment Extract , Lactobacillus/Honeysuckle Flower Extract Ferment Filtrate, Stearic Acid, Tremella Fuciformis Sporocarp Extract, Beeswax, Arginine, Tocopheryl Acetate, Acetyl Hexapeptide-8, Carbomer, Xanthan Gum, Disodium EDTA, Aurantium Dulcis (Orange) Oil, Aniba Rosaeodora (Rosewood) Wood Oil, Lavandula Angustifolia (Lavender) Oil, Rosmarinus Officinalis (Rosemary) Leaf Oil, Foeniculum Vulgare (Fennel) Oil, Citrus Limon (Lemon) Fruit Oil

PURPOSE

Purpose: Skin Protectant

WARNINGS

1. Stop usage immediately if any of the below symptoms occur. Continued use could aggravate symptoms, so it is advisable to consult with a dermatologist immediately. 1) Symptoms include but not limited to: red spots, swelling, itchiness. 2) When having the same symptoms as above due to direct sunlight. 2. Do not apply to areas affected by dermatitis, eczema or wounds. 3. Storage and handling: 1) Tightly close lid after each use. 2 Keep out of reach of children 3) Store in a cool dry area, away from sunlight

KEEP OUT OF REACH OF CHILDREN

Usage

Usage: Take an appropriate amount and gently apply on the face.

Usage

Usage: Take an appropriate amount and gently apply on the face.